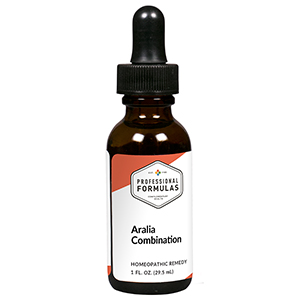 DRUG LABEL: Aralia Combination
NDC: 63083-9256 | Form: LIQUID
Manufacturer: Professional Complementary Health Formulas
Category: homeopathic | Type: HUMAN OTC DRUG LABEL
Date: 20190815

ACTIVE INGREDIENTS: AMERICAN GINSENG 1 [hp_X]/29.5 mL; AVENA SATIVA FLOWERING TOP 3 [hp_X]/29.5 mL; YOHIMBINE 3 [hp_X]/29.5 mL; GALIUM APARINE WHOLE 8 [hp_X]/29.5 mL; SEMPERVIVUM TECTORUM LEAF 8 [hp_X]/29.5 mL; AVISCUMINE 8 [hp_X]/29.5 mL; CINCHONA OFFICINALIS BARK 10 [hp_X]/29.5 mL; COLCHICUM AUTUMNALE BULB 10 [hp_X]/29.5 mL; CONIUM MACULATUM FLOWERING TOP 10 [hp_X]/29.5 mL; GOLDENSEAL 10 [hp_X]/29.5 mL; WOOD CREOSOTE 10 [hp_X]/29.5 mL; PULSATILLA MONTANA WHOLE 10 [hp_X]/29.5 mL; SULFUR 10 [hp_X]/29.5 mL; SCABIES LESION LYSATE (HUMAN) 30 [hp_X]/29.5 mL
INACTIVE INGREDIENTS: ALCOHOL; WATER

R256

ACTIVE INGREDIENTS

Aralia quinquefolia 1X
Avena sativa 3X
Yohimbinum 3X
Galium aparine 8X
Sempervivum tectorum 8X
Viscum album 8X
Cinchona officinalis 10X
Colchicum autumnale 10X
Conium maculatum 10X
Hydrastis canadensis 10X
Kreosotum 10X
Pulsatilla 10X
Sulphur 10X
Psorinum 30X

QUESTIONS

Professional Formulas

PO Box 2034 Lake Oswego, OR 97035

INDICATIONS

For the temporary relief of exhaustion, weakness, or debility.*

PURPOSE

*Claims based on traditional homeopathic practice, not accepted medical evidence. Not FDA evaluated.

WARNINGS

In case of overdose, get medical help or contact a poison control center right away.

Keep out of the reach of children.

PREGNANCY OR BREAST FEEDING

If pregnant or breastfeeding, ask a healthcare professional before use.

DIRECTIONS

Place drops under tongue 30 minutes before/after meals. Adults and children 12 years and over: Take 10 drops up to 3 times per day. Consult a physician for use in children under 12 years of age.

OTHER INFORMATION

Tamper resistant. If seal is broken, do not use. After opening, close container tightly and store at room temperature away from heat.

INACTIVE INGREDIENTS

40% ethanol, purified water.

LABEL

Est 1985

Professional Formulas

Complementary Health

Aralia Combination

Homeopathic Remedy

1 FL. OZ. (29.5 mL)